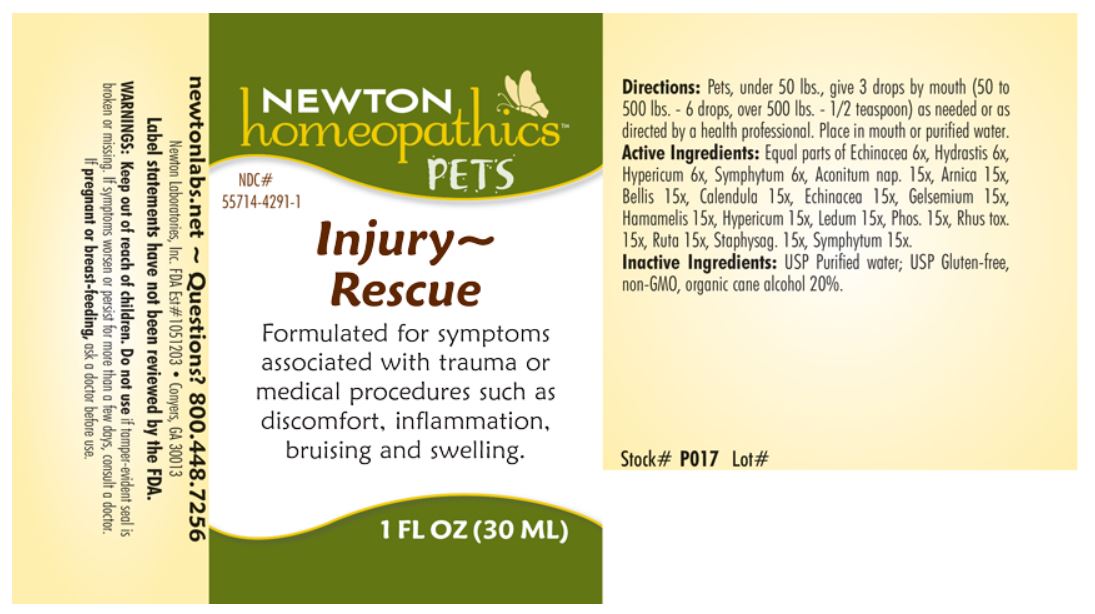 DRUG LABEL: Injury Rescue
NDC: 55714-4291 | Form: LIQUID
Manufacturer: Newton Laboratories, Inc.
Category: homeopathic | Type: OTC ANIMAL DRUG LABEL
Date: 20180228

ACTIVE INGREDIENTS: Aconitum Napellus 15 [hp_X]/1 mL; Arnica Montana 15 [hp_X]/1 mL; Bellis Perennis 15 [hp_X]/1 mL; Calendula Officinalis Flowering Top 15 [hp_X]/1 mL; Echinacea Purpurea 15 [hp_X]/1 mL; Gelsemium Sempervirens Root 15 [hp_X]/1 mL; Hamamelis Virginiana Root Bark/stem Bark 15 [hp_X]/1 mL; Hypericum Perforatum 15 [hp_X]/1 mL; Rhododendron Tomentosum Leafy Twig 15 [hp_X]/1 mL; Phosphorus 15 [hp_X]/1 mL; Toxicodendron Pubescens Leaf 15 [hp_X]/1 mL; Ruta Graveolens Flowering Top 15 [hp_X]/1 mL; Delphinium Staphisagria Seed 15 [hp_X]/1 mL; Comfrey Root 15 [hp_X]/1 mL; Goldenseal 6 [hp_X]/1 mL
INACTIVE INGREDIENTS: Alcohol

Injury-Rescue

PRODUCT NAME & INDICATIONS SECTION

Formulated for symptoms associated with trauma or medical procedures such as discomfort, inflammation, bruising and swelling.

DIRECTION SECTION

Pets, under 50 lbs., give 3 drops by mouth (50 to 500 lbs. - 6 drops, over 500 lbs. - 1/2 teaspoon) as needed or as directed by a health professional. Place in mouth or purified water.

ACTIVE INGREDIENT SECTION

Equal parts of Echinacea 6x, Hydrastis 6x, Hypericum 6x, Symphytum 6x, Aconitum nap. 15x, Arnica 15x, Bellis 15x, Calendula 15x, Echinacea 15x, Gelsemium 15x, Hamamelis 15x, Hypericum 15x, Ledum 15x, Phos. 15x, Rhus tox. 15x, Ruta 15x, Staphysag. 15x, Symphytum 15x.

INACTIVE INGREDIENT SECTION

USP Purified Water; USP Gluten-free, non-GMO, organic cane alcohol 20%.

QUESTIONS SECTION

newtonlabs.net ~ Questions? 800.448.7256 Newton Laboratories, Inc. FDA Est # 1051203 - Conyers, GA 30013

WARNINGS SECTION

WARNINGS: Keep out of reach of children. Do not use if tamper-evident seal is broken or missing. If symptoms worsen or persist for more than a few days, consult a doctor. If pregnant or breast-feeding, ask a doctor before use.

PREGNANCY OR BREAST FEEDING SECTION

If pregnant or breast-feeding, ask a doctor before use.

KEEP OUT OF REACH OF CHILDREN SECTION

Keep out of reach of children.